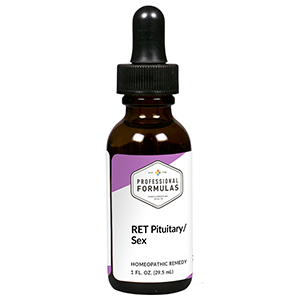 DRUG LABEL: RET Pituitary/Sex
NDC: 63083-7012 | Form: LIQUID
Manufacturer: Professional Complementary Health Formulas
Category: homeopathic | Type: HUMAN OTC DRUG LABEL
Date: 20190815

ACTIVE INGREDIENTS: CICHORIUM INTYBUS FLOWER 3 [hp_X]/29.5 mL; VITIS VINIFERA FLOWERING TOP 3 [hp_X]/29.5 mL; ROSA CANINA FLOWER 3 [hp_X]/29.5 mL; FERROSOFERRIC PHOSPHATE 3 [hp_X]/29.5 mL; POTASSIUM PHOSPHATE, UNSPECIFIED FORM 3 [hp_X]/29.5 mL; SODIUM CHLORIDE 3 [hp_X]/29.5 mL; ACTIVATED CHARCOAL 30 [hp_X]/29.5 mL; CINCHONA BARK 30 [hp_X]/29.5 mL; GELSEMIUM SEMPERVIRENS ROOT 30 [hp_X]/29.5 mL; 1,2-DISTEAROYL-SN-GLYCERO-3-PHOSPHOCHOLINE 30 [hp_X]/29.5 mL; PHOSPHORIC ACID 30 [hp_X]/29.5 mL; SEPIA OFFICINALIS JUICE 30 [hp_X]/29.5 mL; DELPHINIUM STAPHISAGRIA SEED 30 [hp_X]/29.5 mL
INACTIVE INGREDIENTS: ALCOHOL; WATER

RET12

ACTIVE INGREDIENTS

Chicory flower essence 3X
Vine flower essence 3X
Wild rose flower essence 3X
Ferrum phosphoricum 3X, 6X, 30X
Kali phos 3X, 6X, 30X
Nat mur 3X, 6X, 30X
and all the following at 30X, 100X, 200X:
Carbo veg
Cinchona
Gelsemium
Lecithin
Phosphoricum ac
Sepia
Staphysag

QUESTIONS

Professional Formulas

PO Box 2034 Lake Oswego, OR 97035

INDICATIONS

Temporarily relieves apathy, lost motivation, lack of ambition, inflexibility, being authoritative or bullying, self-centered, dissatisfaction, irritability, sadness, anxiousness, or anger.*

PURPOSE

*Claims based on traditional homeopathic practice, not accepted medical evidence. Not FDA evaluated.

WARNINGS

In case of overdose, get medical help or contact a poison control center right away.

Keep out of the reach of children.

PREGNANCY OR BREAST FEEDING

If pregnant or breastfeeding, ask a healthcare professional before use.

DIRECTIONS

Place drops under tongue 30 minutes before/after meals. Adults and children 12 years and over: Take 5 drops up to 4 times per day for up to one month. Consult a physician for use in children under 12 years of age.

OTHER INFORMATION

Tamper resistant. If seal is broken, do not use. After opening, close container tightly and store at room temperature away from heat.

INACTIVE INGREDIENTS

20% ethanol, purified water.

LABEL

Est 1985

Professional Formulas

Complementary Health

RET Pituitary/Sex

Homeopathic Remedy

1 FL. OZ. (29.5 mL)